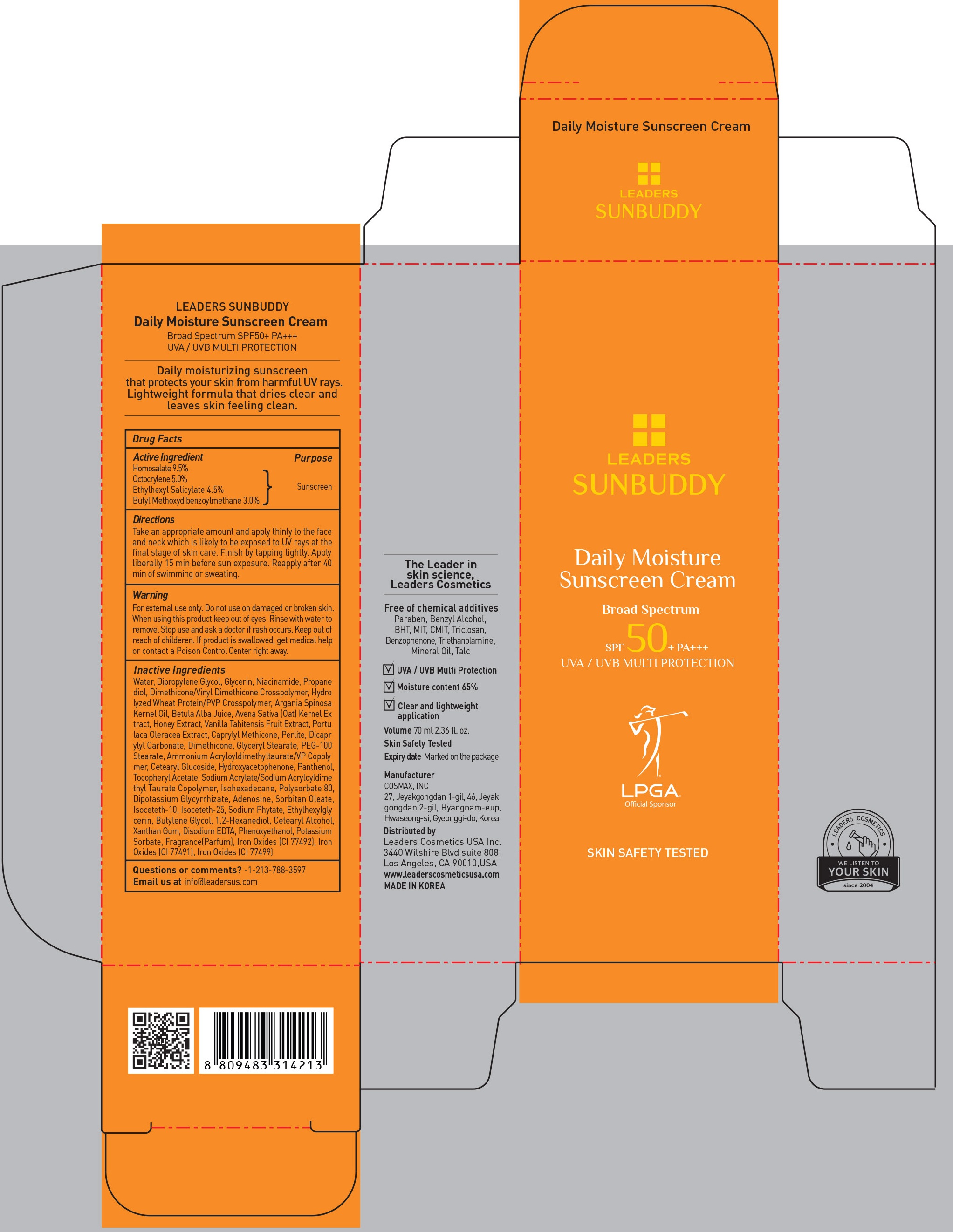 DRUG LABEL: LEADERS SUNBUDDY DAILY MOISTURE SUNSCREEN
NDC: 69424-580 | Form: CREAM
Manufacturer: LEADERS COSMETICS CO.,LTD.
Category: otc | Type: HUMAN OTC DRUG LABEL
Date: 20170222

ACTIVE INGREDIENTS: Homosalate 6.65 g/70 mL; Octocrylene 3.50 g/70 mL; Octisalate 3.15 g/70 mL; Avobenzone 2.10 g/70 mL
INACTIVE INGREDIENTS: Water; Dipropylene Glycol

ACTIVE INGREDIENT

Active Ingredient: Homosalate 9.5%, Octocrylene 5.0%, Ethylhexyl Salicylate 4.5%, Butyl Methoxydibenzoylmethane 3.0%

INACTIVE INGREDIENT

Inactive Ingredients: Water, Dipropylene Glycol, Glycerin, Niacinamide, Propanediol, Dimethicone/Vinyl Dimethicone Crosspolymer, Hydrolyzed Wheat Protein/PVP Crosspolymer, Argania SpinosaKernel Oil, Betula Alba Juice, Avena Sativa (Oat) Kernel Extract, Honey Extract, Vanilla Tahitensis Fruit Extract, Portu laca Oleracea Extract, Caprylyl Methicone, Perlite, Dicaprylyl Carbonate, Dimethicone, Glyceryl Stearate, PEG-100 Stearate, Ammonium Acryloyldimethyltaurate/VP Copolymer, Cetearyl Glucoside, Hydroxyacetophenone, Panthenol, Tocopheryl Acetate, Sodium Acrylate/Sodium Acryloyldimethyl Taurate Copolymer, Isohexadecane, Polysorbate 80, Dipotassium Glycyrrhizate, Adenosine, Sorbitan Oleate, Isoceteth-10, Isoceteth-25, Sodium Phytate, Ethylhexylglycerin, Butylene Glycol, 1,2-Hexanediol, Cetearyl Alcohol, Xanthan Gum, Disodium EDTA, Phenoxyethanol, Potassium Sorbate, Fragrance(Parfum), Iron Oxides (CI 77492), Iron Oxides (CI 77491), Iron Oxides (CI 77499)

PURPOSE

Purpose: Sunscreen

WARNINGS

Warning: For external use only. Do not use on damaged or broken skin. When using this product keep out of eyes. Rinse with water to remove. Stop use and ask a doctor if rash occurs. Keep out of reach of children. If product is swallowed, get medical help or contact a Poison Control Center right away.

Directions

Directions: Take an appropriate amount and apply thinly to the face and neck which is likely to be exposed to UV rays at the final stage of skin care. Finish by tapping lightly. Apply liberally 15 min before sun exposure. Reapply after 40min of swimming or sweating.